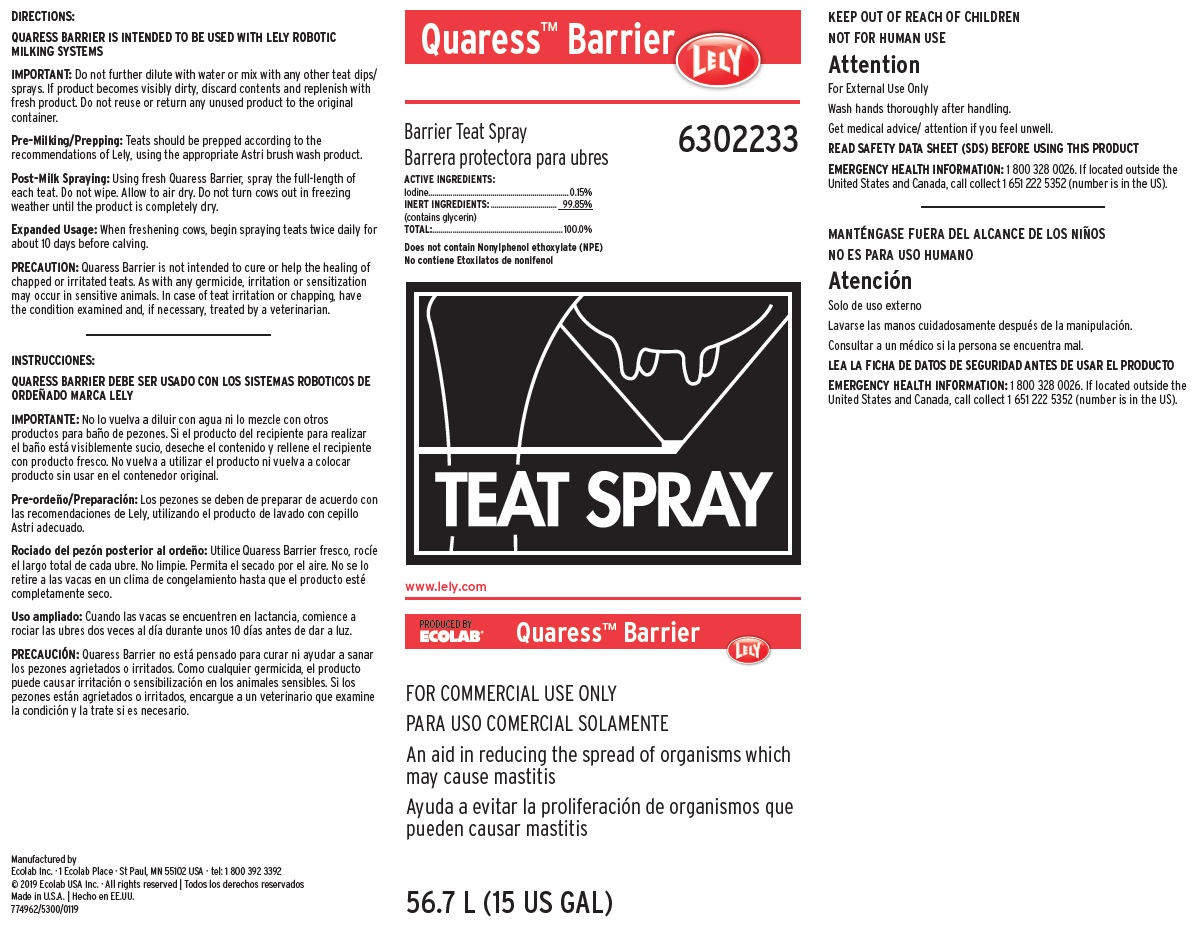 DRUG LABEL: Lely Quaress Barrier
NDC: 47593-603 | Form: SOLUTION
Manufacturer: Ecolab Inc.
Category: animal | Type: OTC ANIMAL DRUG LABEL
Date: 20251116

ACTIVE INGREDIENTS: POVIDONE-IODINE 1.5 mg/1 mL
INACTIVE INGREDIENTS: GLYCERIN

KEEP OUT OF REACH OF CHILDREN

NOT FOR HUMAN USE

Attention

For External Use Only

Wash hands thoroughly after handling.

Get medical advice/ attention if you feel unwell.

DIRECTIONS:

QUARESS BARRIER IS INTENDED TO BE USED WITH LELY ROBOTIC MILKING SYSTEMS

IMPORTANT: Do not further dilute with water or mix with any other teat dips/sprays. If product becomes visibly dirty, discard contents and replenish with fresh product. Do not reuse or return any unused product to the original container.

Pre-Milking/Prepping: Teats should be prepped according to the recommendations of Lely, using the appropriate Astri brush wash product.

Post-Milk Spraying: Using fresh Quaress Barrier, spray the full-length of each teat. Do not wipe. Allow to air dry. Do not turn cows out in freezing weather until the product is completely dry.

Expanded Usage: When freshening cows, begin spraying teats twice daily for about 10 days before calving.

PRECAUTION: Quaress Barrier is not intended to cure or help the healing of chapped or irritated teats. As with any germicide, irritation or sensitization may occur in sensitive animals. In case of teat irritation or chapping, have the condition examined and, if necessary, treated by a veterinarian.

OTHER SAFETY INFORMATION

READ SAFETY DATA SHEET (SDS) BEFORE USING THIS PRODUCT

EMERGENCY HEALTH INFORMATION: 1 800 328 0026. If located outside the United States and Canada, call collect 1 651 222 5352 (number is in the US).

Representative label and principal display panel

Quaress Barrier

Barrier Teat Spray

ACTIVE INGREDIENTS:

Iodine......................................................................0.15%

INERT INGREDIENTS:.................................. 99.85%

(contains glycerin)

TOTAL:................................................................. 100.0%

Does not contain Nonylphenol ethoxylate (NPE)

TEAT SPRAY

FOR COMMERCIAL USE ONLY

An aid in reducing the spread of organisms which may cause mastitis

56.7 L (15 US GAL)

Manufactured by

Ecolab Inc. · 1 Ecolab Place · St Paul, MN 55102 USA · tel: 1 800 392 3392

© 2019 Ecolab USA Inc. · All rights reserved | Todos los derechos reservados

Made in U.S.A. | Hecho en EE.UU.

774962/5300/0119